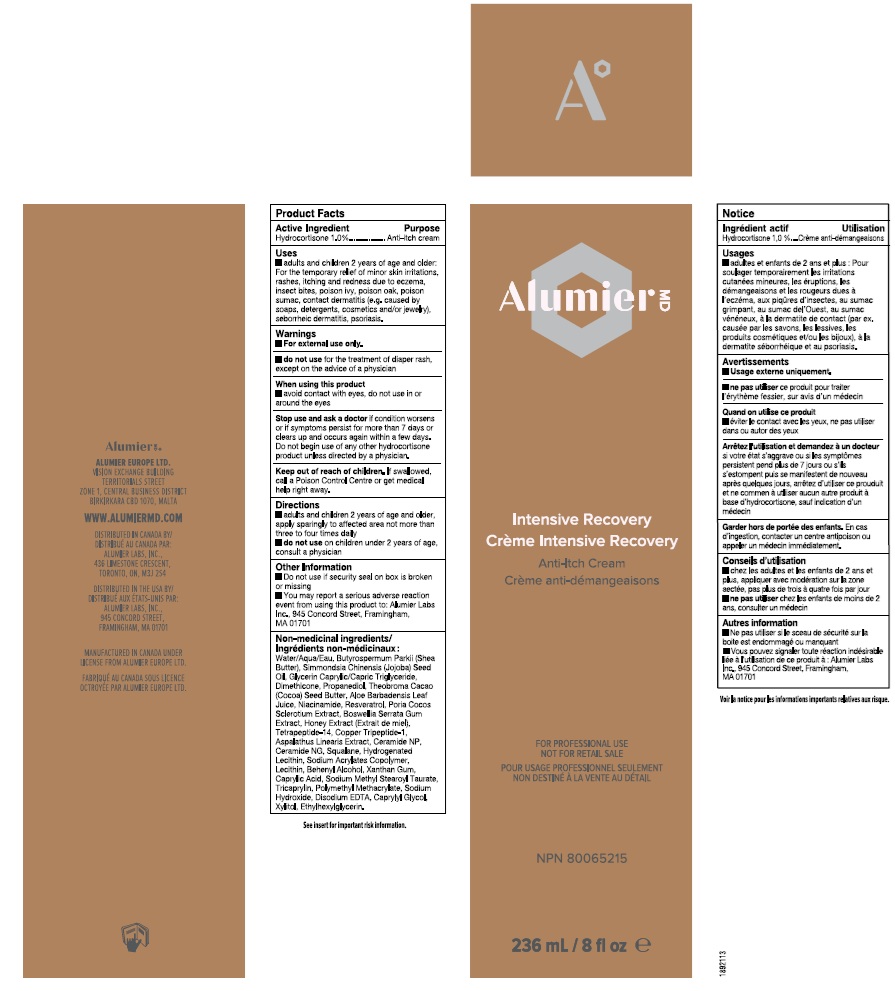 DRUG LABEL: Alumier MD Intensive Recovery
NDC: 69473-017 | Form: CREAM
Manufacturer: Alumier Labs
Category: otc | Type: HUMAN OTC DRUG LABEL
Date: 20250806

ACTIVE INGREDIENTS: HYDROCORTISONE 10 mg/1 mL
INACTIVE INGREDIENTS: CERAMIDE NP; CERAMIDE NG; LECITHIN, SOYBEAN; HYDROGENATED SOYBEAN LECITHIN; TRICAPRYLIN; CAPRYLYL GLYCOL; XYLITOL; HONEY; EDETATE DISODIUM; SODIUM HYDROXIDE; JOJOBA OIL; WATER; SHEA BUTTER; MEDIUM-CHAIN TRIGLYCERIDES; GLYCERIN; DIMETHICONE; PROPANEDIOL; COCOA BUTTER; ALOE VERA LEAF; NIACINAMIDE; RESVERATROL; INDIAN FRANKINCENSE; SQUALANE; ETHYLHEXYLGLYCERIN; POLY(METHYL METHACRYLATE; 450000 MW); XANTHAN GUM; CAPRYLIC ACID; SODIUM METHYL STEAROYL TAURATE; COPPER TRIPEPTIDE-1; WOLFIPORIA COCOS SCLEROTIUM; BEHENYL ALCOHOL

Alumier MD Intensive Recovery

Active Ingredient

Hydrocortisone 1.0%

Purpose

Anti-itch cream

Uses

- adults and children 2 years of age and older: For the temporary relief of minor skin irritations, rashes, itching and redness due to eczema, insect bites, poison ivy, poison oak, poison sumac, contact dermatitis (e.g. caused by soaps, detergents, cosmetics and/or jewelry), seborrheic dermatitis, psoriasis.

Warnings

- For external use only.

- do not use for the treatment of diaper rash, except on the advice of a physician

When using this product

- avoid contact with eyes, do not use in or around the eyes

Stop use and ask a doctor if condition worsens or if symptoms persist for more than 7 days or clears up and occurs again within a few days. Do not begin use of any other hydrocortisone product unless directed by a physician.

Keep out of reach of children. If swallowed, call a Poison Control Centre or get medical help right away.

Directions

- adults and children 2 years of age and older, apply sparingly to affected area not more than three to four times daily
- do not use on children under 2 years of age, consult a physician

Other Information

- Do not use if security seal is broken or missing.
- You may report a serious adverse reaction event from using this product to: Alumier Labs Inc., 945 Concord Street, Framingham, MA 01701

Non-medicinal ingredients

Water/Aqua/Eau, Propanediol, Butyrospermum Parkii (Shea Butter), Simmondsia Chinensis (Jojoba) Seed Oil, Glycerin, Caprylic/Capric Triglyceride, Dimethicone, Propanediol, Theobroma Cacao (Cocoa) Seed Butter, Aloe Barbadensis Leaf Juice, Niacinamide, Resveratrol, Poria Cocos Sclerotium Extract, Boswellia Serrata Gum Extract, Honey Extract (Extrait de miel), Tetrapeptide-14, Copper Tripeptide-1, Aspalathus Linearis Extract, Ceramide NP, Ceramide NG, Squalane, Hydrogenated Lecithin, Sodium Acrylates Copolymer, Lecithin, Behenyl Alcohol, Xanthan Gum, Caprylic Acid, Sodium Methyl Stearoyl Taurate, Tricaprylin, Polymethyl Methacrylate, Sodium Hydroxide, Disodium EDTA, Caprylyl Glycol, Xylitol, Ethylhexylglycerin.